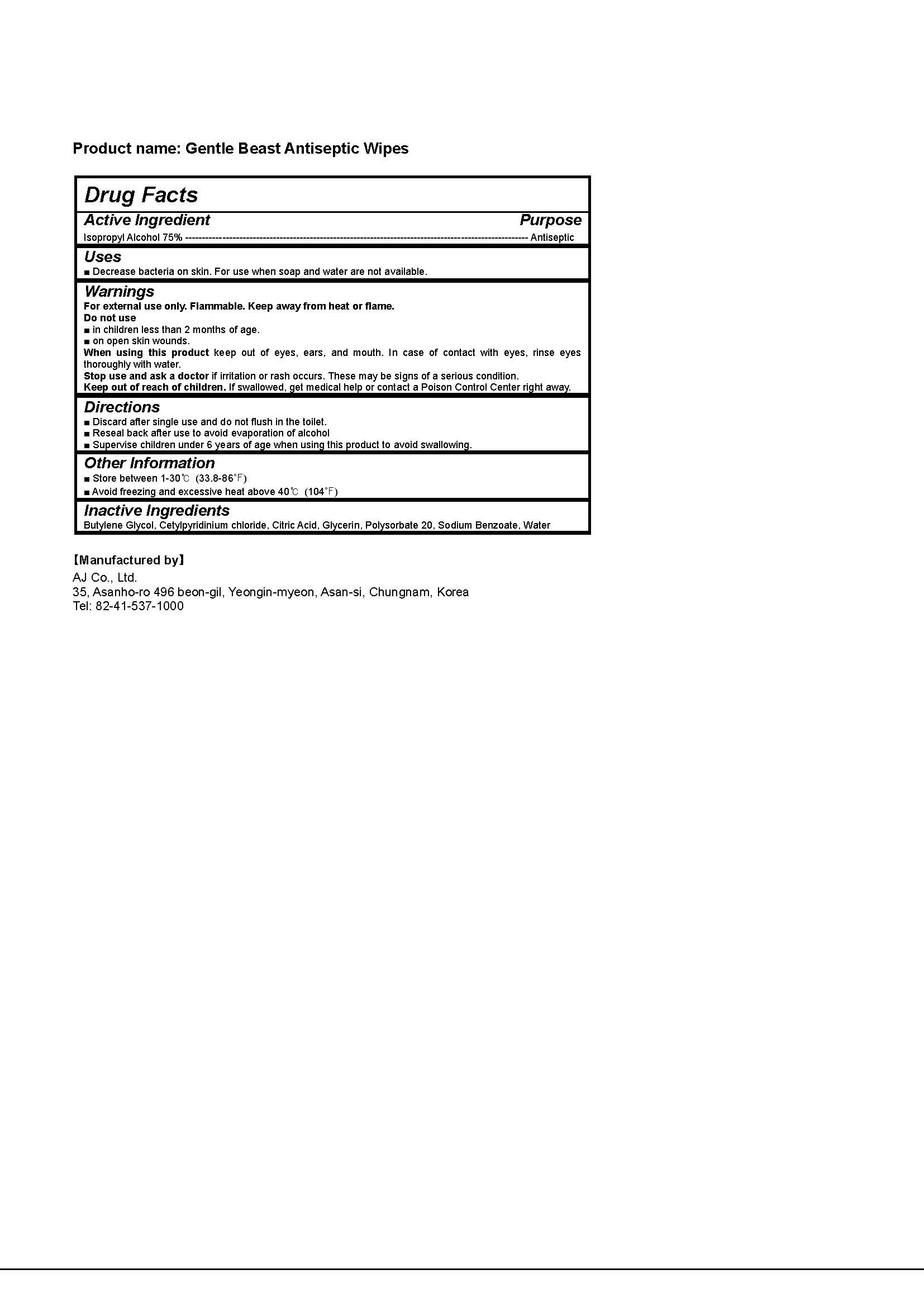 DRUG LABEL: Gentle Beast Antiseptic Wipes
NDC: 75356-0008 | Form: SWAB
Manufacturer: AJ Co., Ltd.
Category: otc | Type: HUMAN OTC DRUG LABEL
Date: 20210316

ACTIVE INGREDIENTS: ISOPROPYL ALCOHOL 75 g/100 g
INACTIVE INGREDIENTS: BUTYLENE GLYCOL; CETYLPYRIDINIUM CHLORIDE; CITRIC ACID MONOHYDRATE; POLYSORBATE 20; GLYCERIN; SODIUM BENZOATE; WATER

AJ Co., Ltd. - Gentle Beast Antiseptic Wipes

ACTIVE INGREDIENT

Isopropyl Alcohol

INACTIVE INGREDIENT

Butylene Glycol, Cetylpyridinium chloride, Citric Acid, Glycerin, Polysorbate 20, Sodium Benzoate, Water

PURPOSE

Decrease bacteria on skin. For use when soap and water are not available.

keep out of reach of the children

INDICATIONS AND USAGE

■ Discard after single use and do not flush in the toilet.

■ Reseal back after use to avoid evaporation of alcohol

■ Supervise children under 6 years of age when using this product to avoid swallowing.

WARNINGS

For external use only. Flammable. Keep away from heat or flame.

Do not use

■ in children less than 2 months of age.

■ on open skin wounds.

When using this product keep out of eyes, ears, and mouth. In case of contact with eyes, rinse eyes thoroughly with water.
Stop use and ask a doctor if irritation or rash occurs. These may be signs of a serious condition.

Keep out of reach of children. If swallowed, get medical help or contact a Poison Control Center right away.

DOSAGE AND ADMINISTRATION

for external use only